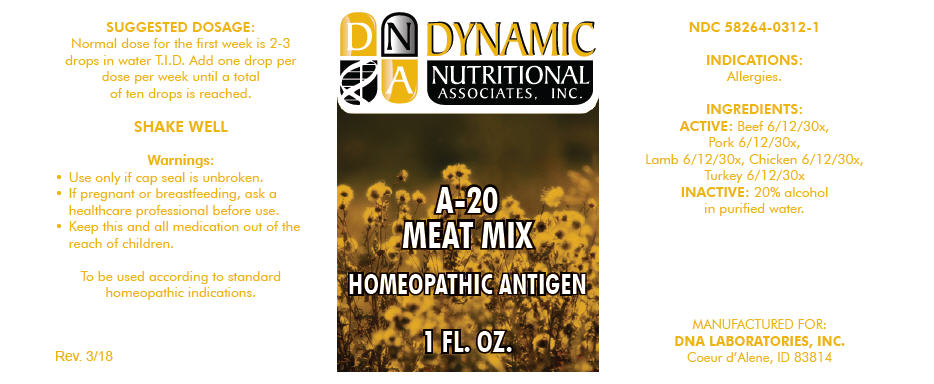 DRUG LABEL: A-20
NDC: 58264-0312 | Form: SOLUTION
Manufacturer: DNA Labs, Inc.
Category: homeopathic | Type: HUMAN OTC DRUG LABEL
Date: 20250109

ACTIVE INGREDIENTS: BEEF 30 [hp_X]/1 mL; PORK 30 [hp_X]/1 mL; LAMB 30 [hp_X]/1 mL; CHICKEN 30 [hp_X]/1 mL; TURKEY 30 [hp_X]/1 mL
INACTIVE INGREDIENTS: ALCOHOL; WATER

A-20

NDC 58264-0312-1

INDICATIONS

PURPOSE

Allergies.

INGREDIENTS

ACTIVE

Beef 6/12/30x, Pork 6/12/30x, Lamb 6/12/30x, Chicken 6/12/30x, Turkey 6/12/30x

INACTIVE

20% alcohol in purified water.

SUGGESTED DOSAGE

Normal dose for the first week is 2-3 drops in water T.I.D. Add one drop per dose per week until a total of ten drops is reached.

STORAGE AND HANDLING

SHAKE WELL

Warnings

- Use only if cap seal is unbroken.

PREGNANCY OR BREAST FEEDING

- If pregnant or breastfeeding, ask a healthcare professional before use.

KEEP OUT OF REACH OF CHILDREN

- Keep this and all medication out of the reach of children.

To be used according to standard homeopathic indications.

PRINCIPAL DISPLAY PANEL - 1 FL. OZ. Bottle Label

DYNAMIC
NUTRITIONAL
ASSOCIATES, INC.

A-20
MEAT MIX

HOMEOPATHIC ANTIGEN

1 FL. OZ.